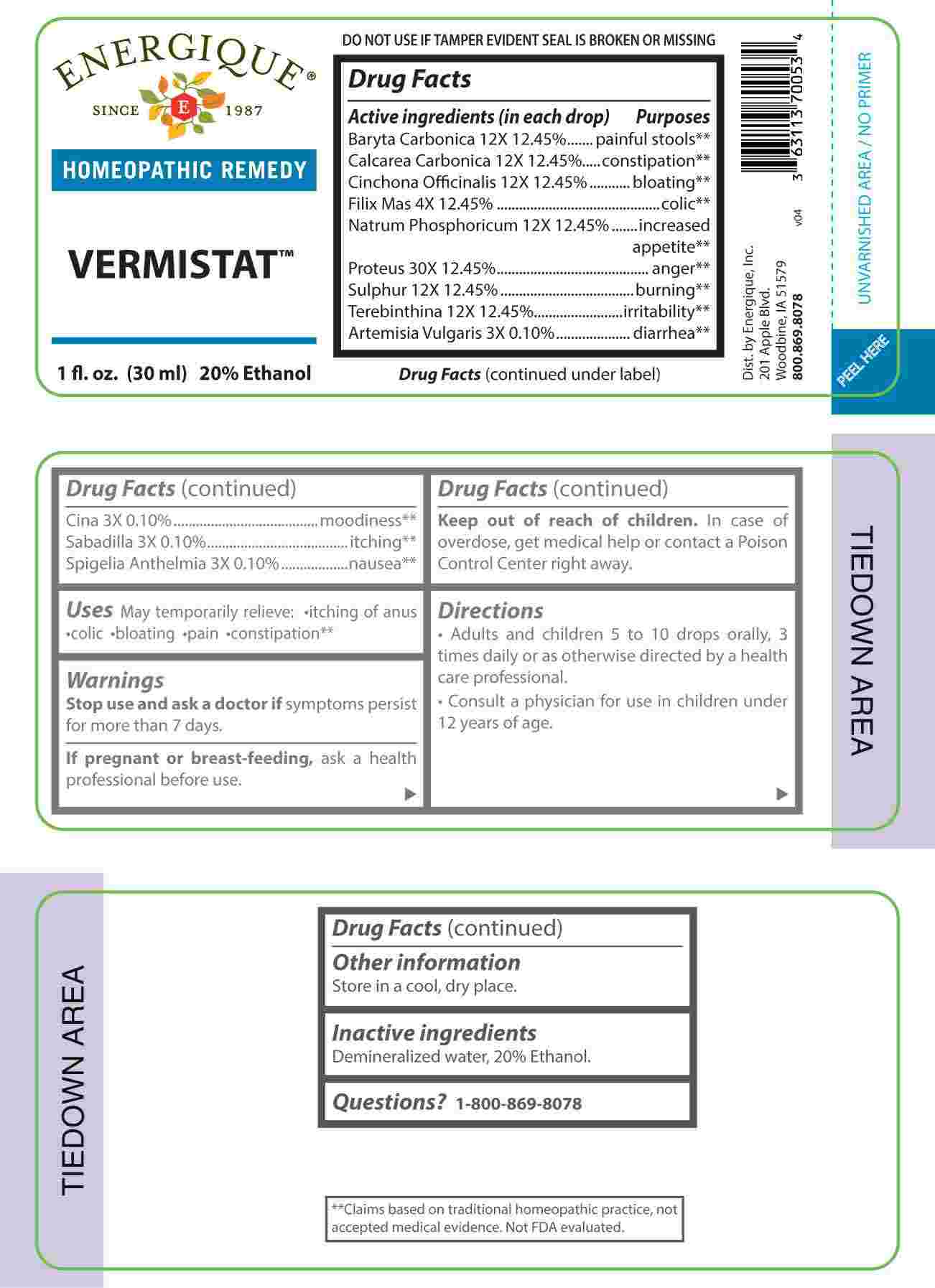 DRUG LABEL: Vermistat
NDC: 44911-0684 | Form: LIQUID
Manufacturer: Energique, Inc.
Category: homeopathic | Type: HUMAN OTC DRUG LABEL
Date: 20231102

ACTIVE INGREDIENTS: ARTEMISIA VULGARIS ROOT 3 [hp_X]/1 mL; ARTEMISIA CINA PRE-FLOWERING TOP 3 [hp_X]/1 mL; SCHOENOCAULON OFFICINALE SEED 3 [hp_X]/1 mL; SPIGELIA ANTHELMIA WHOLE 3 [hp_X]/1 mL; DRYOPTERIS FILIX-MAS ROOT 4 [hp_X]/1 mL; BARIUM CARBONATE 12 [hp_X]/1 mL; OYSTER SHELL CALCIUM CARBONATE, CRUDE 12 [hp_X]/1 mL; CINCHONA OFFICINALIS BARK 12 [hp_X]/1 mL; SODIUM PHOSPHATE, DIBASIC, HEPTAHYDRATE 12 [hp_X]/1 mL; SULFUR 12 [hp_X]/1 mL; TURPENTINE OIL 12 [hp_X]/1 mL; PROTEUS VULGARIS 30 [hp_X]/1 mL
INACTIVE INGREDIENTS: WATER; ALCOHOL

DRUG FACTS:

ACTIVE INGREDIENTS:

(in each drop) Baryta Carbonica 12X 12.45%, Calcarea Carbonica 12X 12.45%, Cinchona Officinalis 12X 12.45%, Filix Mas 4X 12.45%, Natrum Phosphoricum 12X 12.45%, Proteus 30X 12.45%, Sulphur 12X 12.45%, Terebinthina 12X 12.45%, Artemisia Vulgaris 3X 0.10%, Cina 3X 0.10%, Sabadilla 3X 0.10%, Spigelia Anthelmia 3X 0.10%.

PURPOSE:

Baryta Carbonica – painful stools,** Calcarea Carbonica - constipation,** Cinchona Officinalis - bloating,** Filix Mas - colic,** Natrum Phosphoricum – increased appetite,** Proteus - anger,** Sulphur - burning,** Terebinthina - irritability,** Artemisia Vulgaris - diarrhea,** Cina - moodiness,** Sabadilla - itching,** Spigelia Anthelmia - nausea.**

**Claims based on traditional homeopathic practice, not accepted medical evidence. Not FDA evaluated.

USES:

May temporarily relieve: • itching of anus • colic • bloating • pain • constipation**

**Claims based on traditional homeopathic practice, not accepted medical evidence. Not FDA evaluated.

WARNINGS:

Stop use and ask a doctor if symptoms persist for more than 7 days.

If pregnant or breast-feeding, ask a health professional before use.

Keep out of reach of children. In case of overdose, get medical help or contact a Poison Control Center right away.

DO NOT USE IF TAMPER EVIDENT SEAL IS BROKEN OR MISSING

Store in a cool, dry place.

KEEP OUT OF REACH OF CHILDREN:

In case of overdose, get medical help or contact a Poison Control Center right away.

DIRECTIONS:

• Adults and children 5 to 10 drops orally, 3 times daily or as otherwise directed by a health care professional.

• Consult a physician for use in children under 12 years of age.

INACTIVE INGREDIENTS:

Demineralized water, 20% ethanol.

QUESTIONS:

Dist. by Energique, Inc.

201 Apple Blvd

Woodbine, IA 51579

800.869.8078

PACKAGE LABEL DISPLAY:

ENERGIQUE

SINCE 1987

HOMEOPATHIC REMEDY

VERMISTAT

1 fl. oz. (30 ml)